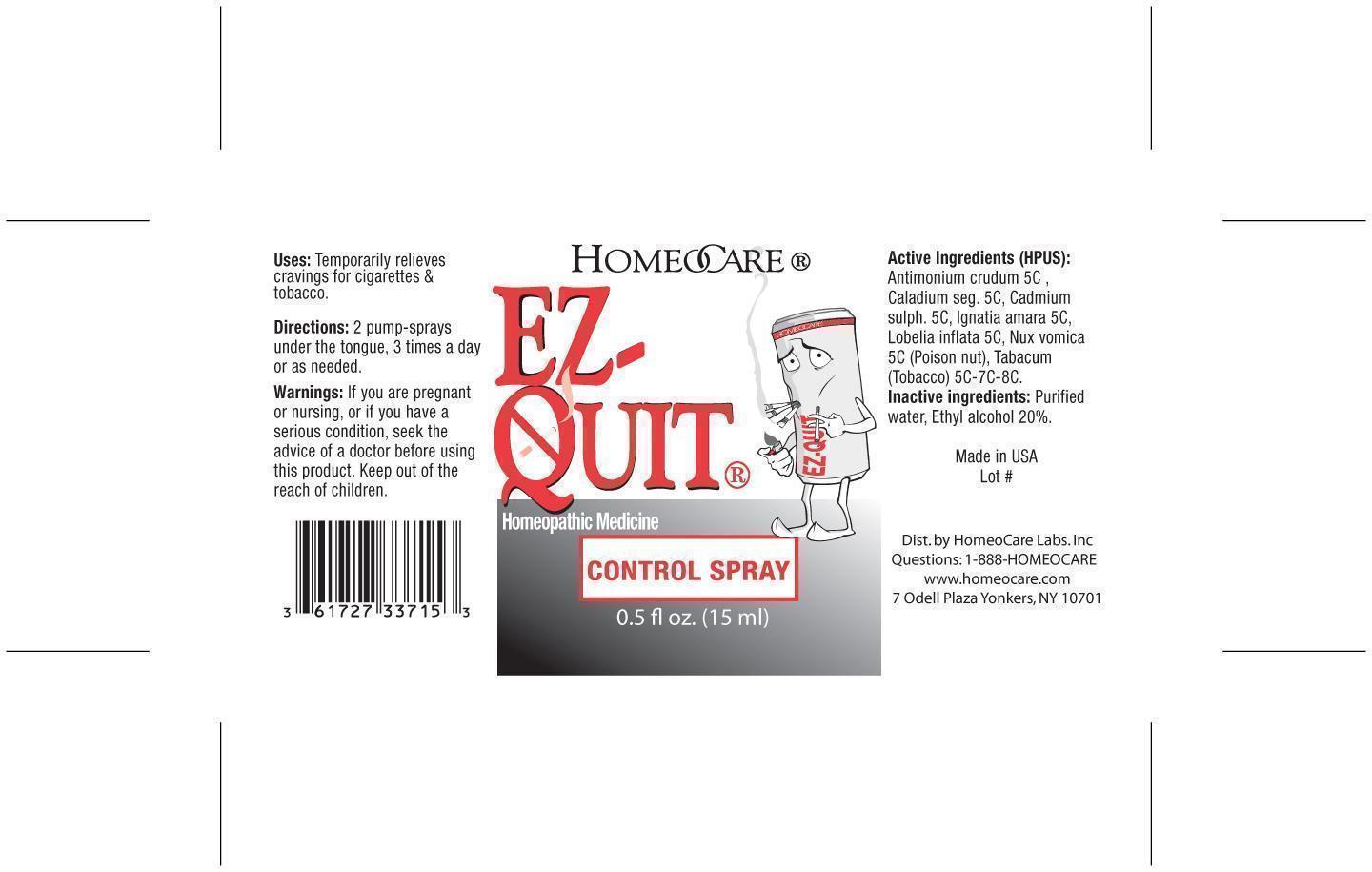 DRUG LABEL: EZ-Quit Control
NDC: 61727-337 | Form: SPRAY
Manufacturer: Homeocare Laboratories
Category: homeopathic | Type: HUMAN OTC DRUG LABEL
Date: 20181231

ACTIVE INGREDIENTS: ANTIMONY TRISULFIDE 5 [hp_C]/15 mL; DIEFFENBACHIA SEGUINE 5 [hp_C]/15 mL; CADMIUM SULFATE 5 [hp_C]/15 mL; STRYCHNOS IGNATII SEED 5 [hp_C]/15 mL; LOBELIA INFLATA 5 [hp_C]/15 mL; STRYCHNOS NUX-VOMICA SEED 5 [hp_C]/15 mL; TOBACCO LEAF 8 [hp_C]/15 mL
INACTIVE INGREDIENTS: WATER; ETHYBENZTROPINE

EZ-Quit Control Spray

Active Ingredients:

Antimonium crudum 5C, Caladium seg. 5C, Cadmium sulph 5C, Ignatia amara 5C, Lobelia inflata 5C, Nux vomica 5C (Poison nut), Tabacum (Tobacco) 5C-7C-8C.

Inactive Ingredients:

Purified water, Ethyl alcohol 20%.

Purpose:

Temporarily relieves cravings for cigarettes & tobacco.

Keep out of reach of children.

Warnings:

If you are pregnant or nursing, or if you have a serious condition, seek the advice of a doctor before using this product. Keep out of the reach of children.

Dosage & Administration:

2 pump-sprays under the tongue, 3 times a day or as needed.

Indications & Usage:

2 pump-sprays under the tongue, 3 times a day as needed.

EZ-Quit Control Spray

Homeopathic Medicine

0.5 fl oz. (15 ml)

EZ-QUIT-Control-Spray.jpg